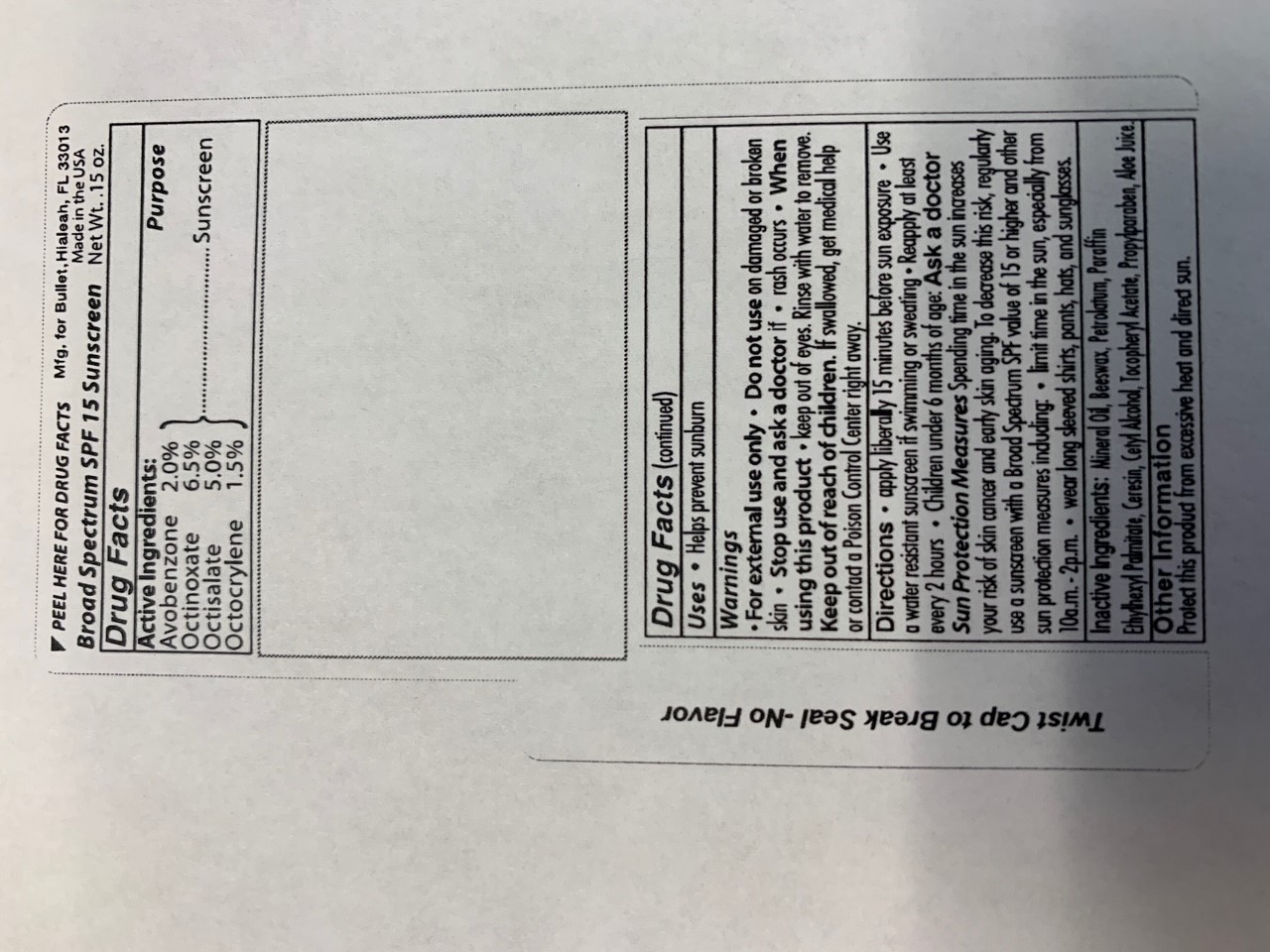 DRUG LABEL: sunscreen
NDC: 19392-310 | Form: LIPSTICK
Manufacturer: Humphreyline
Category: otc | Type: HUMAN OTC DRUG LABEL
Date: 20200528

ACTIVE INGREDIENTS: AVOBENZONE 20 mg/1 g; OCTINOXATE 65 mg/1 g; OCTISALATE 50 mg/1 g; OCTOCRYLENE 15 mg/1 g
INACTIVE INGREDIENTS: PETROLATUM; ETHYLHEXYL PALMITATE; YELLOW WAX; PARAFFIN; MINERAL OIL; CERESIN; CETYL ALCOHOL; ALOE; .ALPHA.-TOCOPHEROL ACETATE; PROPYLPARABEN

Drug Facts

ACTIVE INGREDIENT

Avobenzone (2.0%)

Octinoxate (6.5%)

Octisalate (5.0%)

Octocrylene (1.5%)

PURPOSE

Sunscreen

INDICATIONS AND USAGE

Helps prevent sunburn

INACTIVE INGREDIENT

Mineral Oil, Beeswax, Petrolatum, Paraffin, Ethylhexyl Palmitate, Ceresin, Cetyl Alcohol, Toxopheryl Acetate, Propylparaben, Aloe Juice

WARNINGS

For external use only

Do not use on damaged or broken skin

Stop use and ask a doctor if rash occurs

When using this product, keep out of eyes. Rinse with water to remove

Keep out of reach of children

If swallowed, get medical help or contact a Poison Control Center right away.

DOSAGE AND ADMINISTRATION

Apply liberally 15 min before sun exposure. Use a water resistant sunscreen if swimming or sweating. Reapply at least every 2 hours. Children under 6 months of age: Ask a doctor.

Sun Protection Measures - spending time in the sun increases your risk of skin cancer and early skin aging. To decrease this risk, regularly use a sunscreen with a broad spectrum SPF value of 15 or higher and other sun protection measures including: limit time in the sun, especially from 10am-2pm. Wear long sleeved shirts, pants, hats, and sunglasses.

OTHER SAFETY INFORMATION

Protect this product from excessive heat and direct sun.